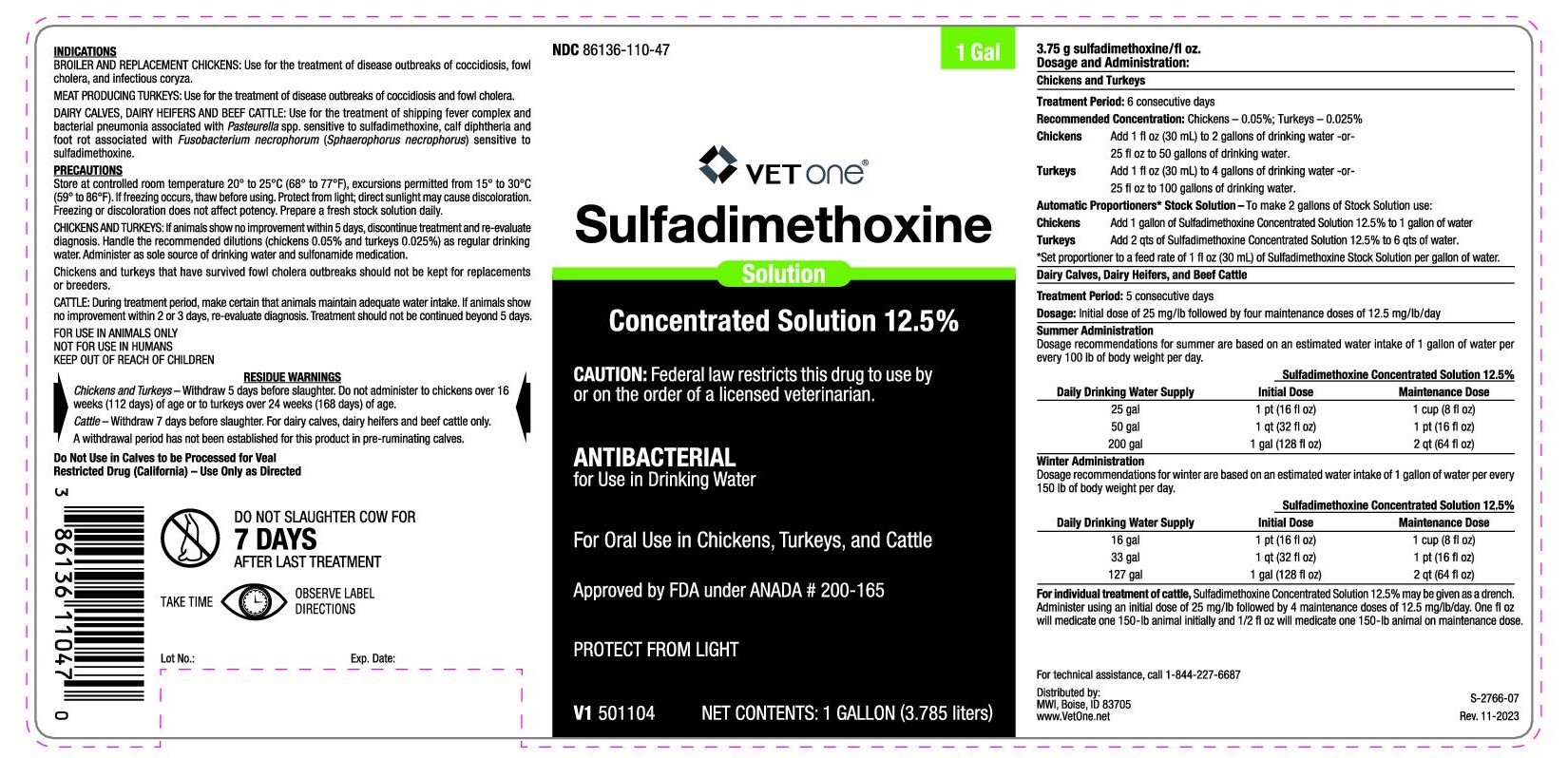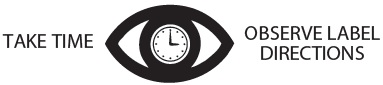 DRUG LABEL: Sulfadimethoxine Concentrated Solution 12.5%
NDC: 86136-110 | Form: SOLUTION
Manufacturer: MWI ANIMAL HELATH
Category: animal | Type: PRESCRIPTION ANIMAL DRUG LABEL
Date: 20231228

ACTIVE INGREDIENTS: Sulfadimethoxine 125 mg/1 mL

Sulfadimethoxine Concentrated Solution 12.5%

NDC: 86136-110-47

Sulfadimethoxine Concentrated Solution 12.5%

ANTIBACTERIAL

for Use in Drinking Water

For Oral Use in Chickens, Turkeys, and Cattle

CAUTION: Federal law restricts this drug to use by or on the order of a licensed veterinarian.

Approved by FDA under ANADA # 200-165

PROTECT FROM LIGHT

NET CONTENTS: 1 Gallon (3.785 L)

INDICATIONS

BROILER AND REPLACEMENT CHICKENS: Use for the treatment of disease outbreaks of coccidiosis, fowl cholera, and infectious coryza.

MEAT PRODUCING TURKEYS: Use for the treatment of disease outbreaks of coccidiosis and fowl cholera.

DAIRY CALVES, DAIRY HEIFERS AND BEEF CATTLE: Use for the treatment of shipping fever complex and bacterial pneumonia associated with Pasteurella spp. sensitive to sulfadimethoxine, calf diphtheria and foot rot associated with Fusobacterium necrophorum (Sphaerophorus necrophorus) sensitive to sulfadimethoxine.

PRECAUTIONS

Store at controlled room temperature 20° to 25°C (68° to 77°F), excursions permitted from 15° to 30°C (59° to 86°F). If freezing occurs, thaw before using. Protect from light; direct sunlight may cause discoloration. Freezing or discoloration does not affect potency. Prepare a fresh stock solution daily.

CHICKENS AND TURKEYS: If animals show no improvement within 5 days, discontinue treatment and re-evaluate diagnosis. Handle the recommended dilutions (chickens 0.05% and turkeys 0.025%) as regular drinking water. Administer as sole source of drinking water and sulfonamide medication.

Chickens and turkeys that have survived fowl cholera outbreaks should not be kept for replacements or breeders.

CATTLE: During treatment period, make certain that animals maintain adequate water intake. If animals show no improvement within 2 or 3 days, re-evaluate diagnosis. Treatment should not be continued beyond 5 days.

FOR USE IN ANIMALS ONLY

NOT FOR USE IN HUMANS

KEEP OUT OF REACH OF CHILDREN

RESIDUE WARNINGS

Chickens and Turkeys – Withdraw 5 days before slaughter. Do not administer to chickens over 16 weeks (112 days) of age or to turkeys over 24 weeks (168 days) of age.

Cattle – Withdraw 7 days before slaughter. For dairy calves, dairy heifers and beef cattle only.

A withdrawal period has not been established for this product in pre-ruminating calves.

Do Not Use in Calves to be Processed for Veal

Restricted Drug (California) – Use Only as Directed

DO NOT SLAUGHTER COW FOR 7 DAYS AFTER LAST TREATMENT

Dosage and Administration

Chickens and Turkeys

Treatment Period: 6 consecutive days

Recommended Concentrations: Chickens – 0.05%; Turkeys – 0.025%

Chickens

Add 1 fl oz (30 mL) to 2 gallons of drinking water or 25 fl oz to 50 gallons of drinking water.

Turkeys

Add 1 fl oz (30 mL) to 4 gallons of drinking water or 25 fl oz to 100 gallons of drinking water.

Automatic Proportioners* Stock Solution

To make 2 gallons of Stock Solution use:

Chickens

Add 1 gallon of Sulfadimethoxine Concentrated Solution 12.5% to 1 gallon of water

Turkeys

Add 2 qts of Sulfadimethoxine Concentrated Solution 12.5% to 6 qts of water

*Set proportioner to a feed rate of 1 fl oz (30 mL) of Sulfadimethoxine Stock Solution per gallon of water.

Dairy Calves, Dairy Heifers, and Beef Cattle

Treatment Period: 5 consecutive days

Dosage: Initial dose of 25 mg/lb followed by four maintenance doses of 12.5 mg/lb/day

Summer Administration

Dosage recommendations for summer are based on an estimated water intake of 1 gallon of water per every 100 lb of body weight per day.

Sulfadimethoxine Concentrated Solution 12.5%

Daily Drinking Water Supply

Initial Dose

Maintenance Dose

25 gal

1 pt (16 fl oz)

1 cup (8 fl oz)

50 gal

1 qt (32 fl oz)

1 pt (16 fl oz)

200 gal

1 gal (128 fl oz)

2 qt (64 fl oz)

Winter Administration

Dosage recommendations for winter are based on an estimated water intake of 1 gallon of water per every 150 lb of body weight per day.

Sulfadimethoxine Concentrated Solution 12.5%

Daily Drinking Water Supply

Initial Dose

Maintenance Dose

16 gal

1 pt (16 fl oz)

1 cup (8 fl oz)

33 gal

1 qt (32 fl oz)

1 pt (16 fl oz)

127 gal

1 gal (128 fl oz)

2 qt (64 fl oz)

For individual treatment of cattle, Sulfadimethoxine Concentrated Solution 12.5% may be given as a drench. Administer using an initial dose of 25 mg/lb followed by 4 maintenance doses of 12.5 mg/lb/day. One fl oz will medicate one 150-lb animal initially and 1/2 fl oz will medicate one 150-lb animal on maintenance dose.